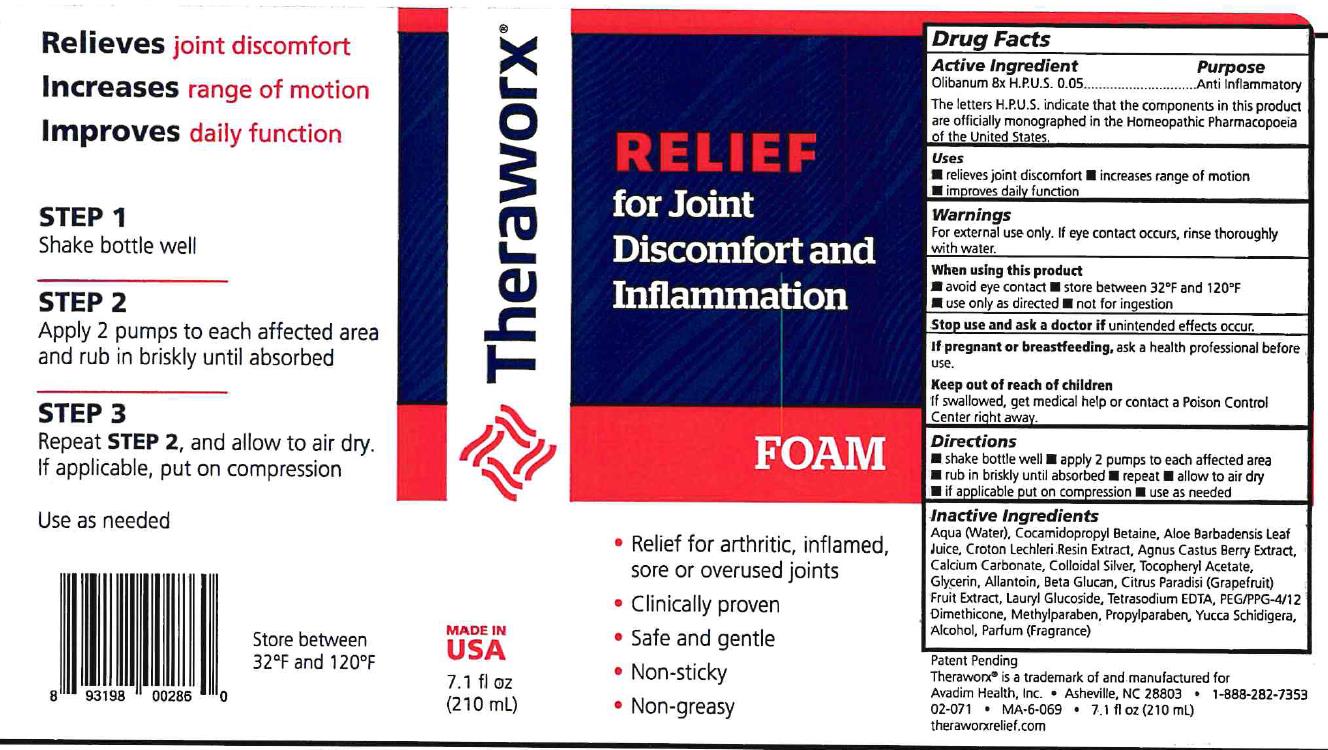 DRUG LABEL: Theraworx Relief Joint Discomfort and Inflamation
NDC: 71064-0013 | Form: SOLUTION
Manufacturer: Relion Manufacturing
Category: homeopathic | Type: HUMAN PRESCRIPTION DRUG LABEL
Date: 20210426

ACTIVE INGREDIENTS: FRANKINCENSE 8 [hp_X]/1 mL
INACTIVE INGREDIENTS: YUCCA SCHIDIGERA WHOLE; GLYCERIN; CROTON LECHLERI RESIN; CALCIUM CARBONATE; ALCOHOL; METHYLPARABEN

Theraworx Joint Discomfort and Inflamation Foam